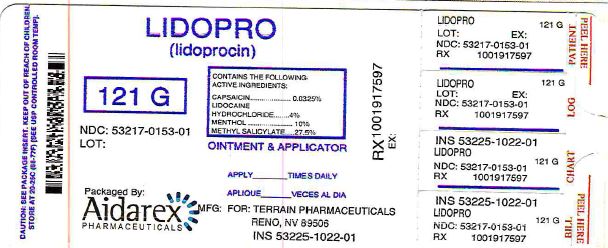 DRUG LABEL: LidoPro
NDC: 53217-153 | Form: OINTMENT
Manufacturer: Aidarex Pharmaceuticals LLC
Category: otc | Type: HUMAN OTC DRUG LABEL
Date: 20170221

ACTIVE INGREDIENTS: CAPSAICIN 0.000325 g/1 g; LIDOCAINE HYDROCHLORIDE 0.04 g/1 g; MENTHOL 0.1 g/1 g; METHYL SALICYLATE 0.275 g/1 g
INACTIVE INGREDIENTS: ALLANTOIN; ALOE VERA LEAF; AMMONIUM ACRYLOYLDIMETHYLTAURATE/VP COPOLYMER; CETYL ALCOHOL; CHAMOMILE; DIMETHICONE; EDETATE DISODIUM; ETHYLHEXYLGLYCERIN; GLYCERIN; GLYCERYL MONOSTEARATE; POLYOXYL 100 STEARATE; TROLAMINE; WATER

LIDOPRO OINTMENT

Active Ingredient

Capsaicin 0.0325%

Purpose

Topical Analgesic

Active Ingredient

Lidocaine HCL 4%

Purpose

Topical Analgesic

Active Ingredient

Menthol 10%

Purpose

Topical Analgesic

Active Ingredient

Methyl Salicylate 27.5%

Purpose

Topical Analgesic

Uses:

Temporarily relieves minor aches and muscles pains associated with:

- arthritis
- simple back pain
- strains
- muscle soreness

Warnings

For external use only

Do not use

- on open wounds, cuts, damaged or infected skin
- with bandage or a heating pad
- if condition worsens or symptoms persists for more than 7 days
- excessive skin irritation occurs

Ask a doctor before use if

- you are allergic to any ingredients, PABA, aspirin products or sulfa

When using this product

- avoid contact with eyes, genitals, and other mucus membranes. If eye contact occurs, rinse thoroughly with water.

If pregnant or breast feeding,

ask a health professional before use.

Keep out of reach of children.

If swallowed, get medical help or contact a Poison Control Center right away. Package not child resistant.

Store

at 20○C - 25○C (68○F - 77○F)

Directions

Adults 18 years and children 12 years and older:

- apply product directly to affected area
- product may be used as necessary, but should not be used more than four times per day.
- wash hands immediately afterwards

Children 12 years or younger: ask a doctor

Inactive Ingredients

Allantoin, Aloe Barbadensis Leaf Juice, Ammonium Acryloyldimethyltaurate/VP Copolymer, Cetyl Alcohol, Chamomilla Recutita Matricaria Flower Extract, Dimethicone, Disodium EDTA, Ethylhexylglycerin, Glycerin, Glyceryl Stearate, Inulin Lauryl Carbamate, PEG-100 Stearate, Phenoxyethanol, Stearic Acid, Triethanolamine, Water.

For Questions or Comments

Please Email info@TerrainRX.com

Manufactured for
Terrain Pharmaceuticals
Reno, NV 89501

Made in the U.S.A.
Patent Pending

Principal Display Panel

SPL Label